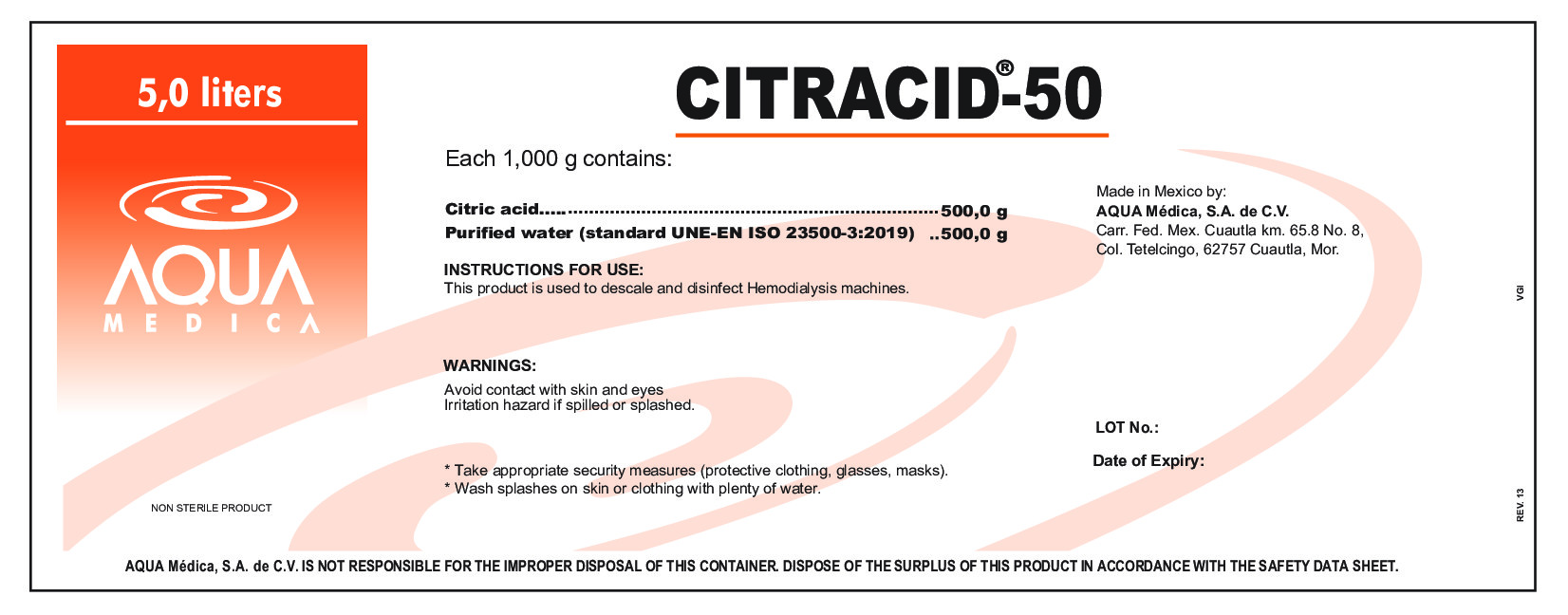 DRUG LABEL: CITRACID-50
NDC: 81943-701 | Form: SOLUTION, CONCENTRATE
Manufacturer: Aqua Medica, S.A. de C.V.
Category: otc | Type: HUMAN OTC DRUG LABEL
Date: 20251110

ACTIVE INGREDIENTS: CITRIC ACID MONOHYDRATE 0.5 g/100 mL
INACTIVE INGREDIENTS: WATER 0.5 g/100 mL

This product is used to descale and desinfect Hemodialysis machines.

ACTIVE INGREDIENT

Citric Acid

PURPOSE

For use with 3-pump hemodialysis machines only.

INDICATIONS AND USAGE

For use with 3-pump hemodialysisi machines only, using purified water (StandardUNE-EN ISO 23500-3:2019).

WARNINGS

Avoid contact with skin an eyes.

Irritation hazard if spilled or splashed.

DO NOT USE

If the warranty seal is damaged or broken and do not allow debris to fall into the concentrate.

WHEN USING

Take appropriate security measures (protective clothing, glasses, masks).

Wash splashes on skin or clothing with plenty of water.

STOP USE

If do not use the entire contents, discard the excess.

Keep out of reach of children. If swallowed, get medical help or contact a Poison Control Center right away.

DOSAGE AND ADMINISTRATION

By diluting one part of this acid concentrate with one part of purified water.

STORAGE AND HANDLING

Store at room temperature.

Keep container tightly closed when not in use.

INACTIVE INGREDIENT

Water.